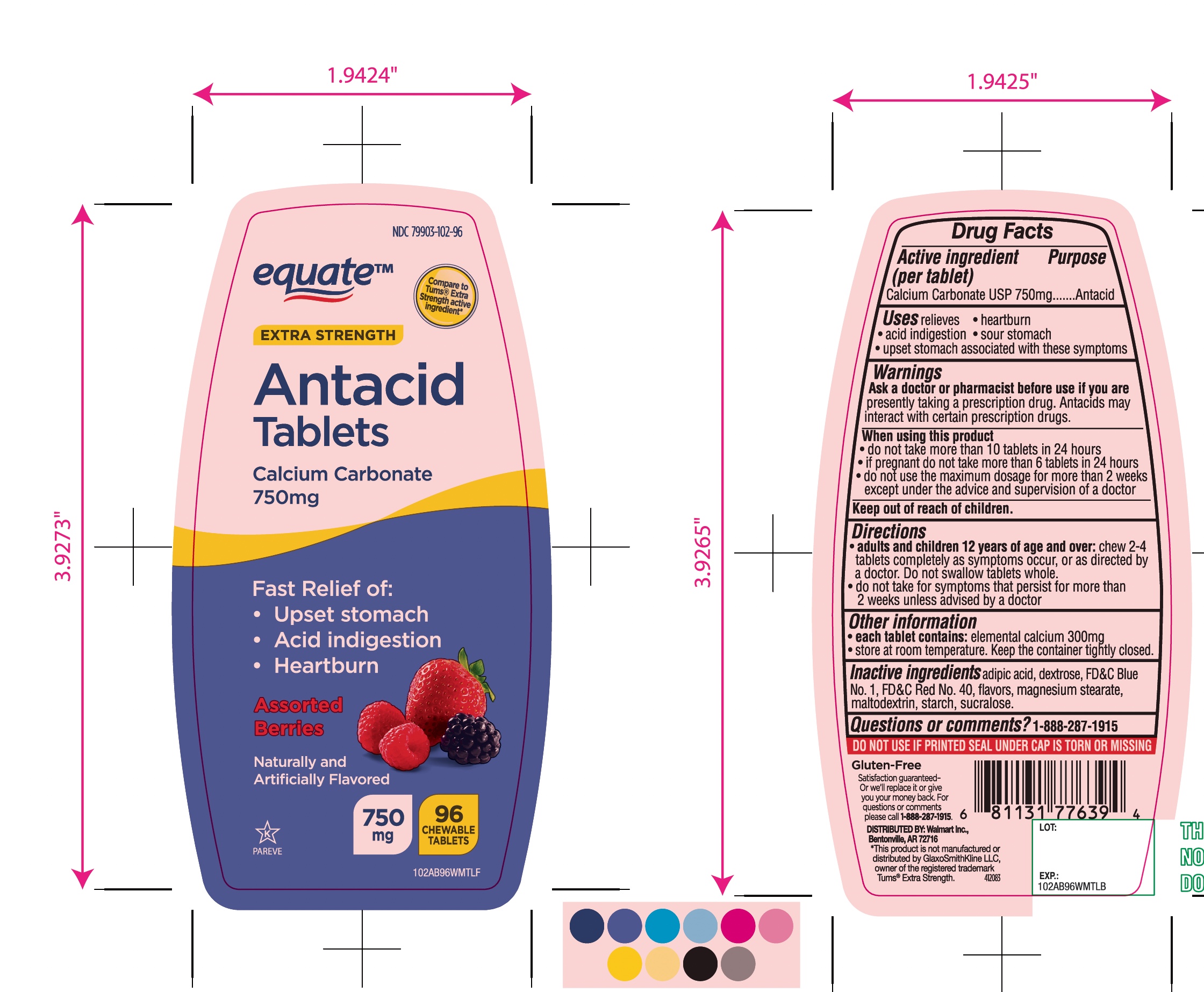 DRUG LABEL: equate Extra Strength

NDC: 79903-102 | Form: TABLET, CHEWABLE
Manufacturer: Wal-Mart Stores,Inc.,
Category: otc | Type: HUMAN OTC DRUG LABEL
Date: 20251027

ACTIVE INGREDIENTS: CALCIUM CARBONATE 750 mg/1 1
INACTIVE INGREDIENTS: ADIPIC ACID; DEXTROSE, UNSPECIFIED FORM; FD&C BLUE NO. 1; FD&C RED NO. 40; MAGNESIUM STEARATE; MALTODEXTRIN; STARCH, CORN; SUCRALOSE

equate Extra Strength Antacid Calcium Carbonate Assorted Berries Chewable Tablets

Active ingredient (per tablet)

Calcium Carbonate USP 750mg

Purpose

Antacid

Uses

relieves

• heartburn

• acid indigestion

• sour stomach

• upset stomach associated with these symptoms

Warnings

Ask a doctor or pharmacist before use if you arepresently taking a prescription drug. Antacids may interact with certain prescription drugs.

When using this product

- do not take more than 10 tablets in 24 hours
- If pregnant do not take more than 6 tablets in 24 hours
- do not use the maximum dosage for more than 2 weeks except under the advice and supervision of a doctor

Directions

- adults and children 12 years of age and over:chew 2-4 tablets completely as symptoms occur, or as directed by a doctor. Do not swallow tablets whole.
- do not take for symptoms that persist for more than 2 weeks unless advised by a doctor

Other Information

• each tablet contains: elemental calcium 300mg

• store at room temperature. Keep the container tightly closed.

Inactive ingredients

adipic acid, dextrose, FD&C Blue No. 1, FD&C Red No. 40, flavors, magnesium stearate, maltodextrin, starch, sucralose.

Questions or comments?

1-888-287-1915

Package/Label Principal Display Panel

NDC 79903-102-96

equate™

Compare to Tums® Extra Strength Active Ingredient*

Extra Strength

Antacid Tablets

Calcium Carbonate 750 mg

Fast Relief of:

- Upset stomach
- Acid indigestion
- Heartburn

Assorted Berries

750 mg

96 CHEWABLE TABLETS

Gluten-Free

Satisfaction guaranteed-

For questions or comments, please call

1-888-287-1915.

Distributed by: Wal-Mart Stores, Inc.,

Bentonville, AR 72716

SAFETY SEALED: DO NOT USE IF PRINTED SEAL UNDER CAP IS TORN OR MISSING

*This product is not manufactured or distributed by GlaxoSmithKline LLC, owner of the registered trademark, Tums®.